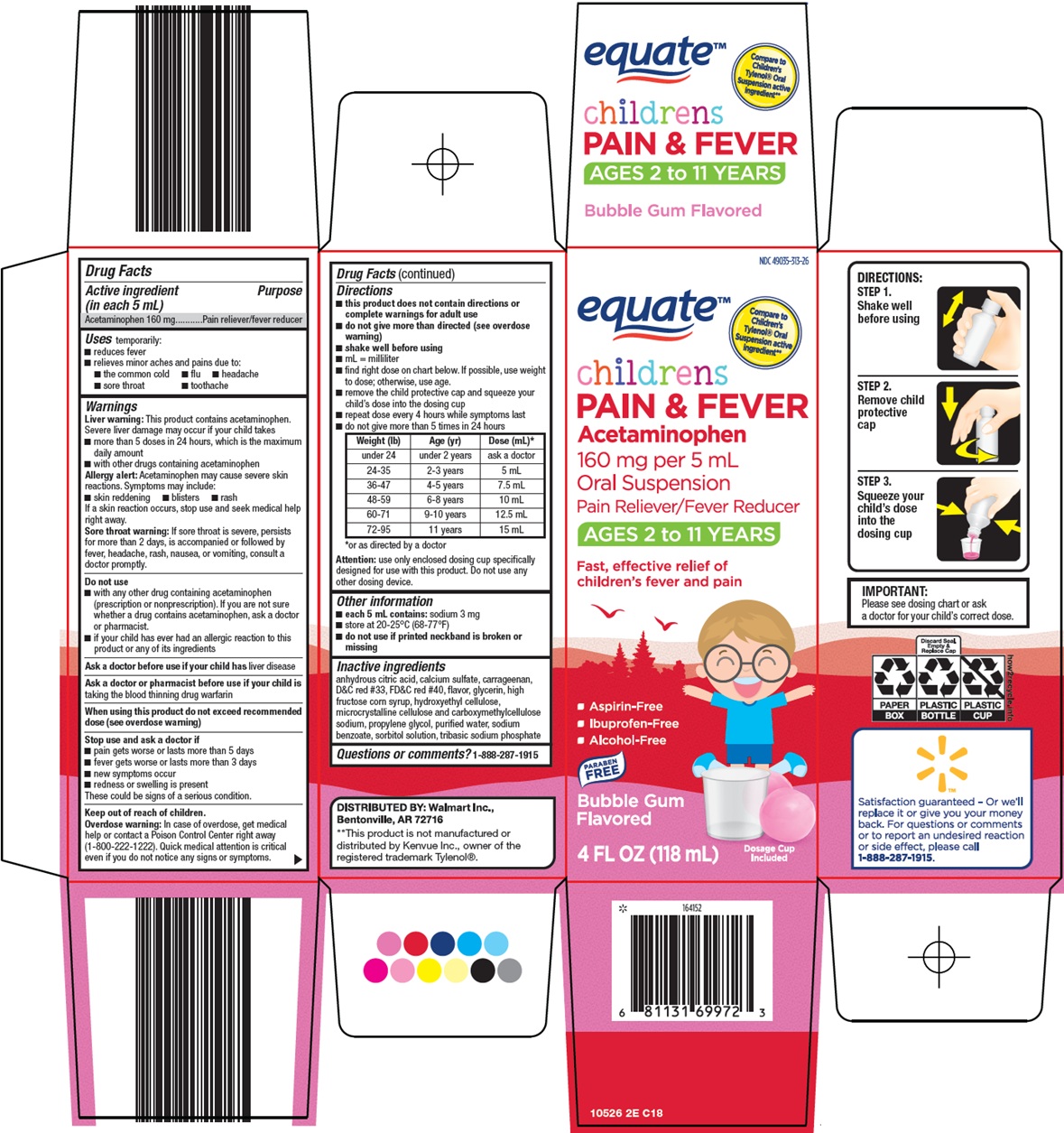 DRUG LABEL: Equate Childrens Pain and Fever
NDC: 49035-313 | Form: SUSPENSION
Manufacturer: Wal-Mart Stores Inc
Category: otc | Type: HUMAN OTC DRUG LABEL
Date: 20260223

ACTIVE INGREDIENTS: ACETAMINOPHEN 160 mg/5 mL
INACTIVE INGREDIENTS: ANHYDROUS CITRIC ACID; CALCIUM SULFATE, UNSPECIFIED FORM; CARRAGEENAN; D&C RED NO. 33; FD&C RED NO. 40; GLYCERIN; HIGH FRUCTOSE CORN SYRUP; HYDROXYETHYL CELLULOSE, UNSPECIFIED; MICROCRYSTALLINE CELLULOSE; CARBOXYMETHYLCELLULOSE SODIUM, UNSPECIFIED; PROPYLENE GLYCOL; WATER; SODIUM BENZOATE; SORBITOL; SODIUM PHOSPHATE, TRIBASIC

Wal-Mart Children’s Pain & Fever Drug Facts

Active ingredient (in each 5 mL)

Acetaminophen 160 mg

Purpose

Pain reliever/fever reducer

Uses

temporarily:

- reduces fever
- relieves minor aches and pains due to:
- the common cold
- flu
- headache
- sore throat
- toothache

Warnings

Liver warning: This product contains acetaminophen. Severe liver damage may occur if your child takes

- more than 5 doses in 24 hours, which is the maximum daily amount
- with other drugs containing acetaminophen

Allergy alert: Acetaminophen may cause severe skin reactions. Symptoms may include:

- skin reddening
- blisters
- rash

If a skin reaction occurs, stop use and seek medical help right away.

Sore throat warning: If sore throat is severe, persists for more than 2 days, is accompanied or followed by fever, headache, rash, nausea, or vomiting, consult a doctor promptly.

Do not use

- with any other drug containing acetaminophen (prescription or nonprescription). If you are not sure whether a drug contains acetaminophen, ask a doctor or pharmacist.
- if your child has ever had an allergic reaction to this product or any of its ingredients

Ask a doctor before use if your child has

liver disease

Ask a doctor or pharmacist

before use if your child is taking the blood thinning drug warfarin

When using this product

do not exceed recommended dose (see overdose warning)

Stop use and ask a doctor if

- pain gets worse or lasts more than 5 days
- fever gets worse or lasts more than 3 days
- new symptoms occur
- redness or swelling is present

These could be signs of a serious condition.

Keep out of reach of children.

Overdose warning: In case of overdose, get medical help or contact a Poison Control Center right away (1-800-222-1222). Quick medical attention is critical even if you do not notice any signs or symptoms.

Directions

- this product does not contain directions or complete warnings for adult use
- do not give more than directed (see overdose warning)
- shake well before using
- mL = milliliter
- find right dose on chart below. If possible, use weight to dose; otherwise, use age.
- remove the child protective cap and squeeze your child’s dose into the dosing cup
- repeat dose every 4 hours while symptoms last
- do not give more than 5 times in 24 hours

Weight (lb) | Age (yr) | Dose (mL)*
under 24 | under 2 years | ask a doctor
24-35 | 2-3 years | 5 mL
36-47 | 4-5 years | 7.5 mL
48-59 | 6-8 years | 10 mL
60-71 | 9-10 years | 12.5 mL
72-95 | 11 years | 15 mL

*or as directed by a doctor

Attention: use only enclosed dosing cup specifically designed for use with this product. Do not use any other dosing device.

Other information

- each 5 mL contains: sodium 3 mg
- store at 20-25°C (68-77°F)
- do not use if printed neckband is broken or missing

Inactive ingredients

anhydrous citric acid, calcium sulfate, carrageenan, D&C red #33, FD&C red #40, flavor, glycerin, high fructose corn syrup, hydroxyethyl cellulose, microcrystalline cellulose and carboxymethylcellulose sodium, propylene glycol, purified water, sodium benzoate, sorbitol solution, tribasic sodium phosphate

Questions or comments?

1-888-287-1915

Principal Display Panel

equate™

Compare to Children’s Tylenol® Oral Suspension active ingredient

children’s PAIN & FEVER

Acetaminophen 160 mg per 5 mL Oral Suspension

Pain Reliever/Fever Reducer

AGES 2 to 11 YEARS

Fast, effective relief of children’s fever and pain

• Aspirin-Free

• Ibuprofen-Free

• Alcohol-Free

PARABEN FREE

Bubble Gum Flavored

4 FL OZ (118 mL)

Dosage Cup Included